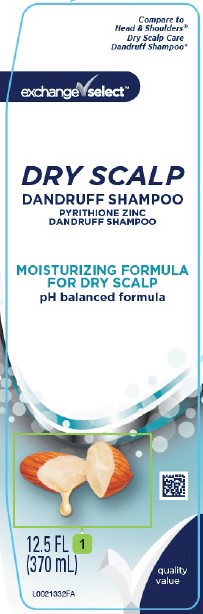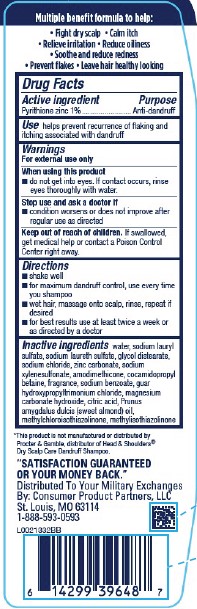 DRUG LABEL: Dandruff

NDC: 55301-281 | Form: SHAMPOO
Manufacturer: Your Military Exchanges
Category: otc | Type: HUMAN OTC DRUG LABEL
Date: 20260212

ACTIVE INGREDIENTS: PYRITHIONE ZINC 10 mg/1 mL
INACTIVE INGREDIENTS: ZINC CARBONATE; SODIUM XYLENESULFONATE; AMODIMETHICONE (800 CST); COCAMIDOPROPYL BETAINE; SODIUM BENZOATE; GUAR HYDROXYPROPYLTRIMONIUM CHLORIDE (1.7 SUBSTITUENTS PER SACCHARIDE); MAGNESIUM CARBONATE HYDROXIDE; CITRIC ACID MONOHYDRATE; ALMOND OIL; METHYLCHLOROISOTHIAZOLINONE; METHYLISOTHIAZOLINONE; WATER; SODIUM LAURYL SULFATE; SODIUM LAURETH SULFATE; GLYCOL DISTEARATE; SODIUM CHLORIDE

Exchange Select 281.007/281AN
Dry Scalp Dandruff Shampoo

Claims

Multiple benefit formula to help:

- Fight dry scalp
- Calm itch
- Relieve irritation
- Reduce oilness
- Soothe and reduce redness
- Prevent flakes
- Leave hair healthy looking

Active Ingredient

Pyrithione zinc 1%

Purpose

Anti-dandruff

Use

helps prevent recurrence of flaking and itching associated with dandruff

Warnings

For external use only

When using this product

- do not get into eyes. If contact occurs, rinse eyes thoroughly with water.

Stop use and ask a docotor if

- condition worsens or does not improve after regular use as directed

Keep out of reach of children.

If swallowed, get medical help or contact a Poison Control Center right away.

Directions

- shake well
- for maximum dandruff control, use every time you shampoo
- wet hair, massage onto scalp, rinse, repeat if desired
- for best results use at least twice a week or as directed by a doctor

Inactive ingredients

water, sodium lauryl sulfate, sodium laureth sulfate, glycol distearate, sodium chloride, zinc carbonate, sodium xylenesulfonate, amodimethicone, cocamidopropyl betaine, fragrance, sodium benzoate, guar hydroxypropyltrimonium chloride, magnesium carbonate hydroxide, citric acid, Prunus amygdalus dulcis (sweet almond) oil, methylchloroisothiazolinone, methylisothiazolinone

disclaimer

*This product is not manufactured or distributed by Procter & Gamble, distributor of Head & Shoulders® Dry Scalp Care Dandruff Shampoo.

Adverse Reactions Section

"SATISFACTION GUARANTEED OR YOUR MONEY BACK."

Distributed To Your Military Exchanges

By: Consumer Product Partners, LLC

St. Louis, MO 63114

1-888-593-0593

principal display panel

Compare to Head & Shoulders

Dry Scalp Care Dandruff Shampoo*

exchange select™

DRY SCALP

DANDRUFF SHAMPOO

PYRITHIONE ZINC

DANDRUFF SHAMPOO

MOISTURIZING FORMULA

FOR DRY SCALP

pH balanced formula

12.5 FL OZ (370 mL)

quality value